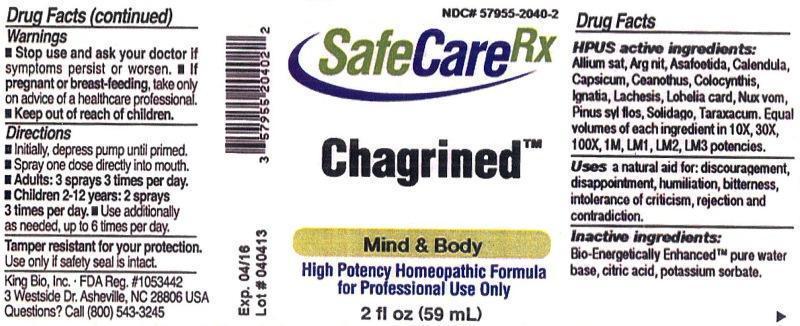 DRUG LABEL: Chagrined
NDC: 57955-2040 | Form: LIQUID
Manufacturer: King Bio Inc.
Category: homeopathic | Type: HUMAN PRESCRIPTION DRUG LABEL
Date: 20130520

ACTIVE INGREDIENTS: GARLIC 10 [hp_X]/59 mL; SILVER NITRATE 10 [hp_X]/59 mL; ASAFETIDA 10 [hp_X]/59 mL; CALENDULA OFFICINALIS FLOWERING TOP 10 [hp_X]/59 mL; CAPSICUM 10 [hp_X]/59 mL; CEANOTHUS AMERICANUS LEAF 10 [hp_X]/59 mL; CITRULLUS COLOCYNTHIS FRUIT PULP 10 [hp_X]/59 mL; STRYCHNOS IGNATII SEED 10 [hp_X]/59 mL; LACHESIS MUTA VENOM 10 [hp_X]/59 mL; LOBELIA CARDINALIS 10 [hp_X]/59 mL; STRYCHNOS NUX-VOMICA SEED 10 [hp_X]/59 mL; PINUS SYLVESTRIS FLOWERING TOP 10 [hp_X]/59 mL; SOLIDAGO VIRGAUREA FLOWERING TOP 10 [hp_X]/59 mL; TARAXACUM OFFICINALE 10 [hp_X]/59 mL
INACTIVE INGREDIENTS: WATER; CITRIC ACID MONOHYDRATE; POTASSIUM SORBATE

Chagrined
SafeCare RX

Drug Facts

______________________________________________________________________________________________________________________

HPUS active ingredients:

Allium sativum, Argentum nitricum, Asafoetida, Calendula officinalis, Capsicum annuum, Ceanothus americanus, Colocynthis, Ignatia amara, Lachesis mutus, Lobelia cardinalis, Nux vomica, Pinus sylvestris, flos, Solidago virgaurea, Taraxacum officinale.

Equal volumes of each ingredient in 10X, 30X, 100X, 1M, LM1, LM2, LM3 potencies.

INDICATIONS AND USAGE

Uses a natural aid for: discouragement, disappointment, humiliation, bitterness, intolerance of criticism, rejection and contradiction.

Inactive ingredients:

Bio-Energetically Enhanced™ pure water base, citric acid, potassium sorbate.

Warnings

- Stop use and ask your doctor if symptoms persist or worsen.
- If pregnant or breast-feeding, take only on advice of a healthcare professional.

Tamper resistant for your protection. Use only if safety seal is intact.

Keep out of reach of children.

Directions

- Initially, depress pump until primed.
- Spray one dose directly into mouth.
- Adults: 3 sprays 3 times per day.
- Children 2-12 years: 2 sprays 3 times per day.
- Use additionally as needed, up to 6 times per day.

Purpose

Uses a natural aid for:

- discouragement
- disappointment
- humiliation
- bitterness
- intolerance of criticism
- rejection
- contradiction